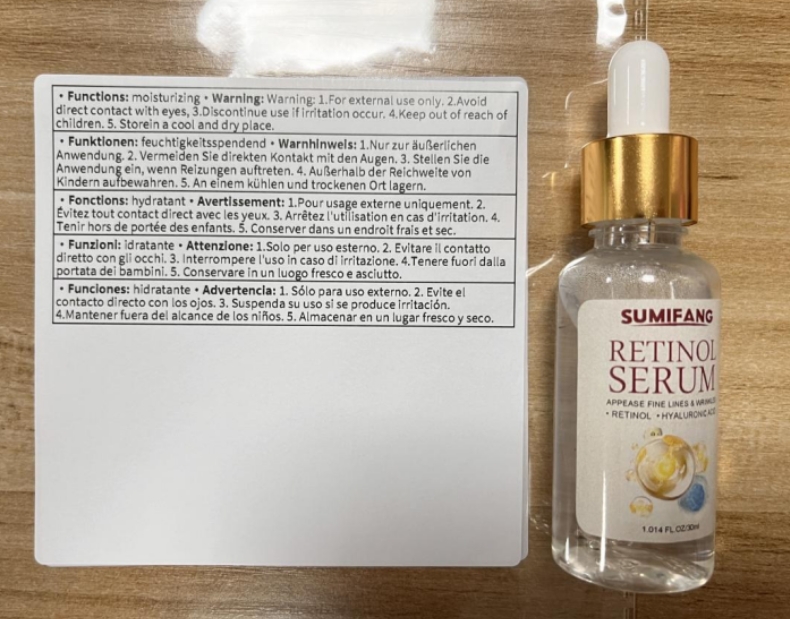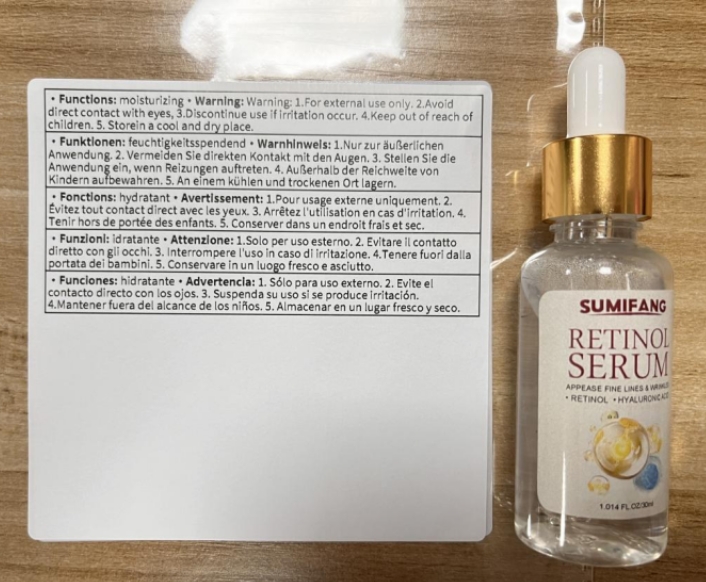 DRUG LABEL: RETINOL SERUM
NDC: 84025-083 | Form: LOTION
Manufacturer: Guangzhou Yanxi Biotechnology Co., Ltd
Category: otc | Type: HUMAN OTC DRUG LABEL
Date: 20240723

ACTIVE INGREDIENTS: NIACINAMIDE 5 mg/100 mL; BETAINE SALICYLATE 3 mg/100 mL
INACTIVE INGREDIENTS: WATER

DOSAGE AND ADMINISTRATION

DAB on your face after washing

WARNINGS

keep out of children

INACTIVE INGREDIENT

Aqua

INDICATIONS AND USAGE

Face dehydrated

keep out of children

PURPOSE

Moisturize face, even complexion